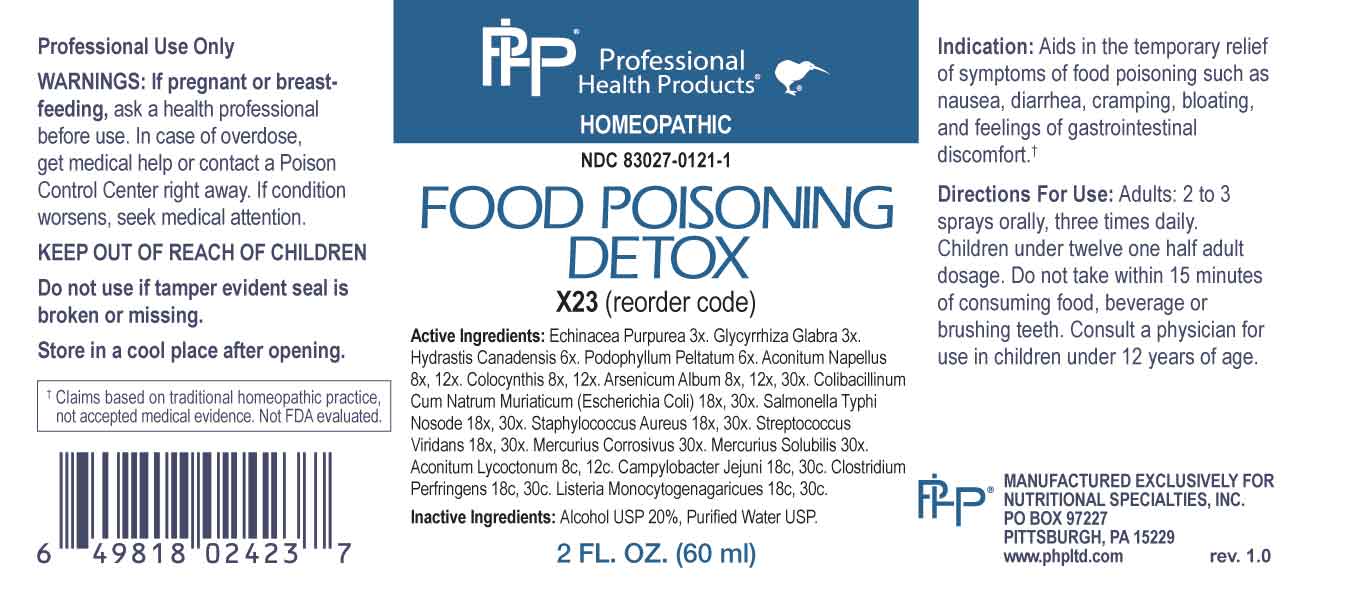 DRUG LABEL: Food Poisoning Detox
NDC: 83027-0121 | Form: SPRAY
Manufacturer: Nutritional Specialties, Inc.
Category: homeopathic | Type: HUMAN OTC DRUG LABEL
Date: 20231101

ACTIVE INGREDIENTS: ECHINACEA PURPUREA WHOLE 3 [hp_X]/1 mL; GLYCYRRHIZA GLABRA 3 [hp_X]/1 mL; GOLDENSEAL 6 [hp_X]/1 mL; PODOPHYLLUM 6 [hp_X]/1 mL; ACONITUM NAPELLUS WHOLE 8 [hp_X]/1 mL; CITRULLUS COLOCYNTHIS FRUIT PULP 8 [hp_X]/1 mL; ARSENIC TRIOXIDE 8 [hp_X]/1 mL; ESCHERICHIA COLI 18 [hp_X]/1 mL; SALMONELLA ENTERICA ENTERICA SEROVAR TYPHI 18 [hp_X]/1 mL; STAPHYLOCOCCUS AUREUS 18 [hp_X]/1 mL; STREPTOCOCCUS VIRIDANS GROUP 18 [hp_X]/1 mL; MERCURIC CHLORIDE 30 [hp_X]/1 mL; MERCURIUS SOLUBILIS 30 [hp_X]/1 mL; ACONITUM LYCOCTONUM WHOLE 8 [hp_C]/1 mL; CAMPYLOBACTER JEJUNI 18 [hp_C]/1 mL; CLOSTRIDIUM PERFRINGENS 18 [hp_C]/1 mL; LISTERIA MONOCYTOGENES 18 [hp_C]/1 mL
INACTIVE INGREDIENTS: WATER; ALCOHOL

DRUG FACTS:

ACTIVE INGREDIENTS:

Echinacea Purpurea 3X, Glycyrrhiza Glabra 3X, Hydrastis Canadensis 6X, Podophyllum Peltatum 6X, Aconitum Napellus 8X, 12X, Colocynthis 8X, 12X, Arsenicum Album 8X, 12X, 30X, Colibacillinum Cum Natrum Muriaticum (Escherichia Coli) 18X, 30X, Salmonella Typhi Nosode 18X, 30X, Staphylococcus Aureus 18X, 30X, Streptococcus Viridans 18X, 30X, Mercurius Corrosivus 30X, Mercurius Solubilis 30X, Aconitum Lycoctonum 8C, 12C, Campylobacter Jejuni 18C, 30C, Clostridium Perfringens 18C, 30C, Listeria Monocytogenes 18C, 30C.

PURPOSE:

Aids in temporary relief of symptoms of food poisoning such as nausea, diarrhea, cramping, bloating, and feelings of gastrointestinal†

†Claims based on traditional homeopathic practice, not accepted medical evidence. Not FDA evaluated.

WARNINGS:

Professional Use Only

If pregnant or breast-feeding, ask a health professional before use.

In case of overdose, get medical help or contact a Poison Control Center right away.

If condition worsens, seek medical attention.

KEEP OUT OF REACH OF CHILDREN

Do not use if tamper evident seal is broken or missing.

Store in a cool place after opening

KEEP OUT OF REACH OF CHILDREN:

In case of overdose, get medical help or contact a Poison Control Center right away.

DIRECTIONS:

Adults: 2 to 3 sprays orally, three times daily. Children under twelve one half adult dosage. Do not take within 15 minutes of consuming food, beverage or brushing teeth. Consult a physician for use in children under 12 years of age.

INDICATIONS:

Aids in temporary relief of symptoms of food poisoning such as nausea, diarrhea, cramping, bloating, and feelings of gastrointestinal†

†Claims based on traditional homeopathic practice, not accepted medical evidence. Not FDA evaluated.

INACTIVE INGREDIENTS:

Alcohol USP 20%, Purified Water USP.

QUESTIONS:

MANUFACTURED EXCLUSIVELY FOR

NUTRITIONAL SPECIALTIES, INC.

PO BOX 97227

PITTSBURG, PA 15229

www.phpltd.com

PACKAGE LABEL DISPLAY:

Professional

Health Products

HOMEOPATHIC

NDC 83027-0121-1

FOOD POISONING

DETOX

2 FL. OZ (60 ml)

F